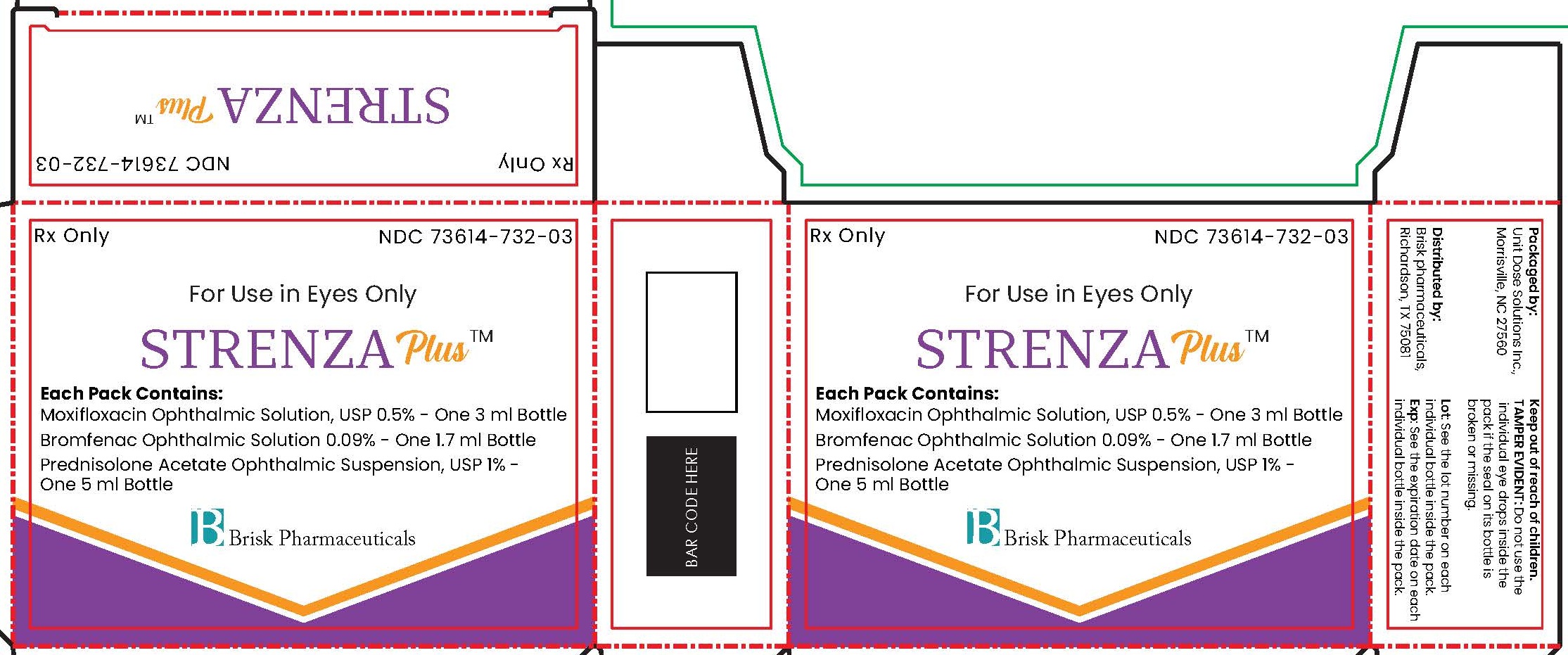 DRUG LABEL: STRENZA PLUS
NDC: 73614-732 | Form: KIT | Route: OPHTHALMIC
Manufacturer: Brisk Pharmaceuticals
Category: prescription | Type: HUMAN PRESCRIPTION DRUG LABEL
Date: 20250212

ACTIVE INGREDIENTS: MOXIFLOXACIN HYDROCHLORIDE MONOHYDRATE 5 mg/1 mL; PREDNISOLONE ACETATE 10 mg/1 mL; BROMFENAC SODIUM 0.9 mg/1 mL
INACTIVE INGREDIENTS: BORIC ACID; WATER; HYDROCHLORIC ACID; SODIUM HYDROXIDE; SODIUM CHLORIDE; BENZALKONIUM CHLORIDE; POLYSORBATE 80; WATER; SODIUM HYDROXIDE; CITRIC ACID MONOHYDRATE; EDETATE DISODIUM; HYPROMELLOSE, UNSPECIFIED; SODIUM PHOSPHATE, DIBASIC, UNSPECIFIED FORM; GLYCERIN; WATER; POVIDONE K30; SODIUM SULFITE; BENZALKONIUM CHLORIDE 0.05 mg/1 mL; BORIC ACID; POLYSORBATE 80; EDETATE DISODIUM; SODIUM BORATE; SODIUM HYDROXIDE

STRENZA PLUS

DESCRIPTION

Rx Only

NDC 73614-732-03

For Use in Eyes Only

STRENZA Plus ™

Each Pack Contains:

Moxifloxacin Ophthalmic Solution, USP 0.5% - One 3 ml Bottle

Bromfenac Ophthalmic Solution 0.09% - One 1.7 ml Bottle

Prednisolone Acetate Ophthalmic Suspension, USP 1% - One 5 ml Bottle

Brisk Pharmaceuticals

DESCRIPTION

Packaged by:

Unit Dose Solutions Inc.,

Morrisville, NC 27560

Distributed by:

Brisk pharmaceuticals,

Richardson, TX 75081

Keep out of reach of children.

TAMPER EVIDENT: Do not use the individual eye drops inside the pack if the seal on its bottle is broken or missing.

Lot: See the lot number on each individual bottle inside the pack.

Exp: See the expiration date on each individual bottle inside the pack.